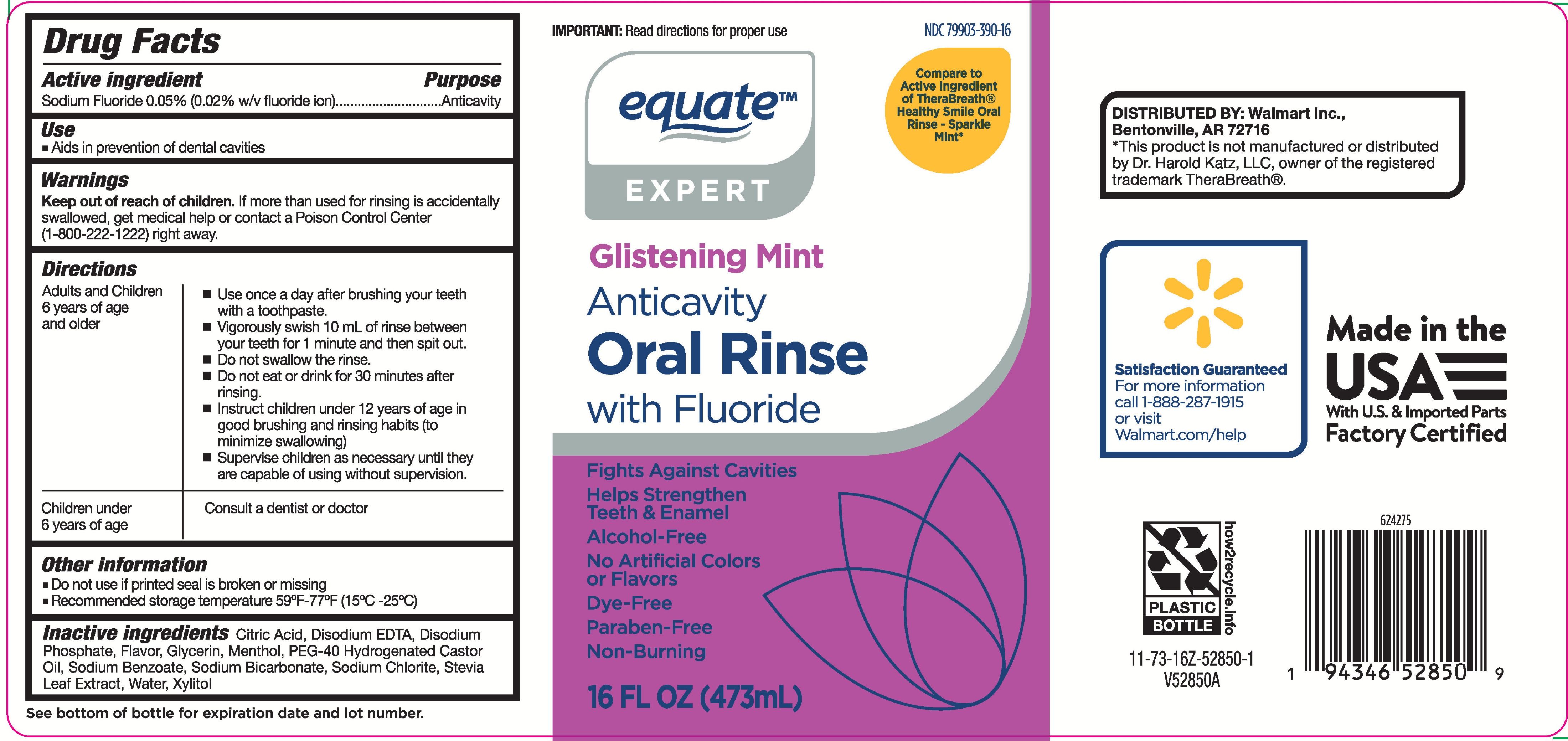 DRUG LABEL: Equate Glistening Mint
NDC: 79903-390 | Form: RINSE
Manufacturer: Walmart Inc.
Category: otc | Type: HUMAN OTC DRUG LABEL
Date: 20251003

ACTIVE INGREDIENTS: SODIUM FLUORIDE 0.005 mg/10 mL
INACTIVE INGREDIENTS: CITRIC ACID; GLYCERIN; EDETATE DISODIUM; PEG-40 HYDROGENATED CASTOR OIL; SODIUM CHLORITE; STEVIA REBAUDIANA LEAF; XYLITOL; SODIUM BICARBONATE; WATER; DISODIUM PHOSPHATE; MENTHOL; SODIUM BENZOATE

Equate Glistening Mint Anticavity Oral Rinse

Active ingredient

Sodium Fluoride

Purpose

Anticavity

Use

- Aids in prevention of dental cavities

Warnings

Keep out of reach of children.

If more than used for rinsing is accidently swallowed, get medical help or contact a Poison Control Center (1-800-222-1222) right away.

Directions

Adults and Children 6 years of age and older:

- Use once a day after brushing your teeth with a toothpaste
- Vigorously swish 10 mL of rinse between your teeth for 1 minute and then spit out
- Do not swallow the rinse
- Do not eat or drink for 30 minutes after rinsing
- Instruct children under 12 years of age in good brushing and rinsing habits (to minimize swallowing)
- Supervise children as necessary until they are capable of using without supervision

Children under 6 years of age: Consult a dentist or doctor

Other information

- Do not use if printed seal is broken or missing
- Recommended storage temperature 59°F-77°F (15°C-25°C)

Inactive ingredients

Citric Acid, Disodium EDTA, Disodium Phosphate, Flavor, Glycerin, Menthol, PEG-40 Hydrogenated Castor Oil, Sodium Benzoate, Sodium Bicarbonate, Sodium Chlorite, Stevia Leaf Extract, Water, Xylitol